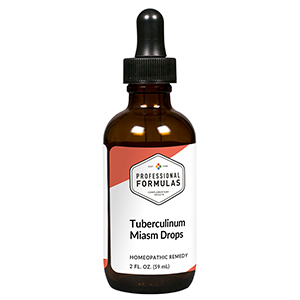 DRUG LABEL: Tuberculinum Miasm Drops
NDC: 63083-2141 | Form: LIQUID
Manufacturer: Professional Complementary Health Formulas
Category: homeopathic | Type: HUMAN OTC DRUG LABEL
Date: 20190815

ACTIVE INGREDIENTS: BAPTISIA TINCTORIA WHOLE 30 [hp_X]/59 mL; OYSTER SHELL CALCIUM CARBONATE, CRUDE 30 [hp_X]/59 mL; CALCIUM SULFATE ANHYDROUS 30 [hp_X]/59 mL; QUININE ARSENITE 30 [hp_X]/59 mL; FERROSOFERRIC PHOSPHATE 30 [hp_X]/59 mL; IODINE 30 [hp_X]/59 mL; POTASSIUM CARBONATE 30 [hp_X]/59 mL; WOOD CREOSOTE 30 [hp_X]/59 mL; PHOSPHORUS 30 [hp_X]/59 mL; SPONGIA OFFICINALIS SKELETON, ROASTED 30 [hp_X]/59 mL; TIN 30 [hp_X]/59 mL; THERIDION CURASSAVICUM 30 [hp_X]/59 mL; BOVINE TUBERCULIN 30 [hp_X]/59 mL; ESCHERICHIA COLI 200 [hp_X]/59 mL
INACTIVE INGREDIENTS: ALCOHOL; WATER

C141

ACTIVE INGREDIENTS

Baptisia tinctoria 30X
Calcarea carbonica 30X
Calcarea sulphurica 30X
Chininum arsenicosum 30X
Ferrum phosphoricum 30X
Iodium 30X
Kali carbonicum 30X
Kreosotum 30X
Phosphorus 30X
Spongia tosta 30X
Stannum metallicum 30X
Theridion 30X
Tuberculinum 30X, 60X, 100X
Bacillinum 200X

QUESTIONS

Professional Formulas

PO Box 2034 Lake Oswego, OR 97035

INDICATIONS

For the temporary relief of cough, congestion, shortness of breath, minor joint pain or inflammation, fatigue, or dissatisfaction consistent with classical tuberculinum miasm.*

PURPOSE

*Claims based on traditional homeopathic practice, not accepted medical evidence. Not FDA evaluated.

WARNINGS

In case of overdose, get medical help or contact a poison control center right away.

Keep out of the reach of children.

PREGNANCY OR BREAST FEEDING

If pregnant or breastfeeding, ask a healthcare professional before use.

DIRECTIONS

Place drops under tongue 30 minutes before/after meals. Adults and children 12 years and over: Take 10 drops up to 3 times per day. Consult a physician for use in children under 12 years of age.

OTHER INFORMATION

Tamper resistant. If seal is broken, do not use. After opening, close container tightly and store at room temperature away from heat.

INACTIVE INGREDIENTS

20% ethanol, purified water.

LABEL

Est 1985

Professional Formulas

Complementary Health

Tuberculinum Miasm Drops

Homeopathic Remedy

2 FL. OZ. (59 mL)